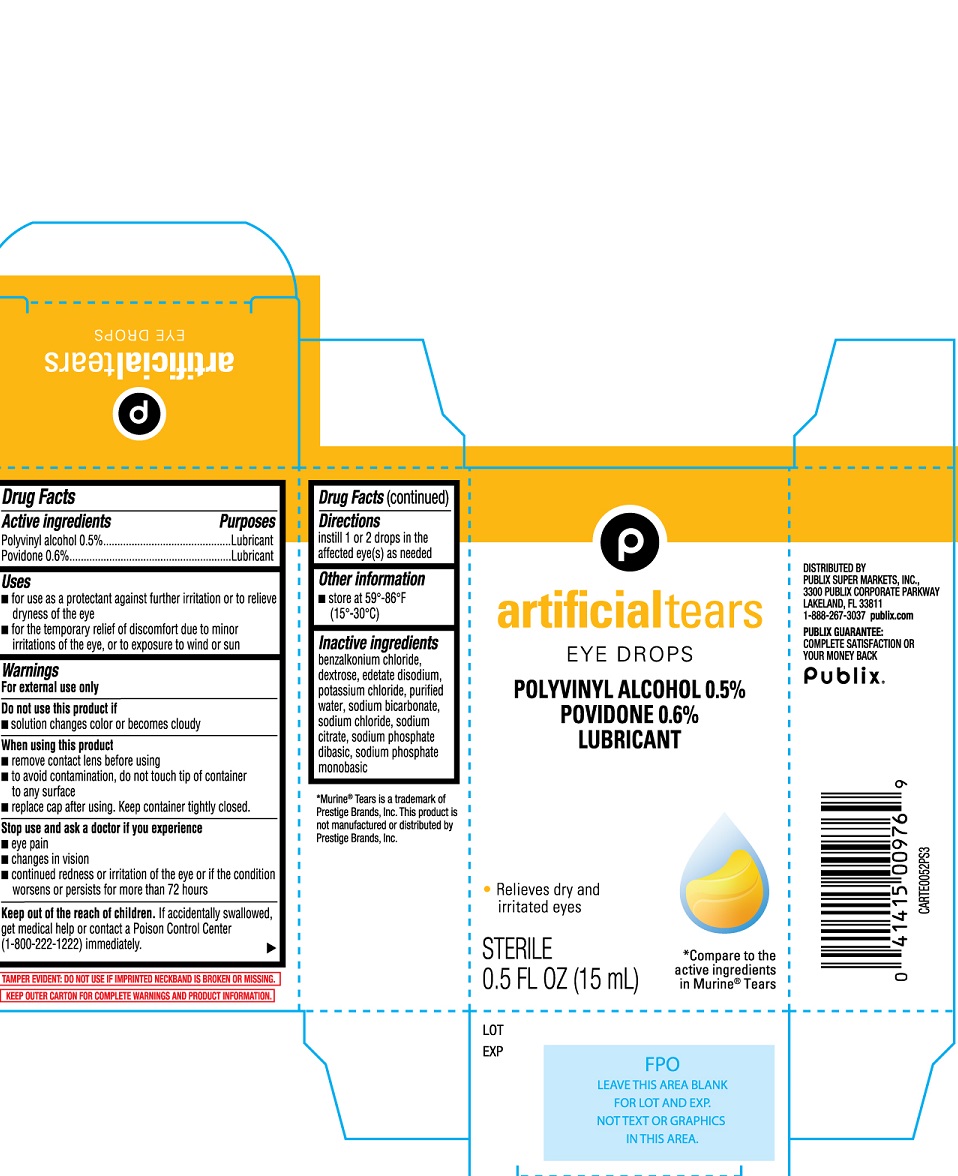 DRUG LABEL: Publix Artificial Tears Eye Drops
NDC: 56062-666 | Form: SOLUTION/ DROPS
Manufacturer: Publix Super Markets, Inc.
Category: otc | Type: HUMAN OTC DRUG LABEL
Date: 20251230

ACTIVE INGREDIENTS: POLYVINYL ALCOHOL 500 mg/100 mL; POVIDONE 600 mg/100 mL
INACTIVE INGREDIENTS: BENZALKONIUM CHLORIDE; DEXTROSE; EDETATE DISODIUM; POTASSIUM CHLORIDE; WATER; SODIUM BICARBONATE; SODIUM CHLORIDE; SODIUM CITRATE; SODIUM PHOSPHATE, DIBASIC; SODIUM PHOSPHATE, MONOBASIC

Publix Artificial Tears 15mL (PLD)

Active ingredients

Polyvinyl alcohol 0.5%

Povidone 0.6%

Purpose

Polyvinyl alcohol: Eye Lubricant

Povidone: Eye Lubricant

Uses:

- for use as a protectant against further irritation or to relieve dryness of the eye
- for the temporary relief of discomfort due to minor irritations of the eye, or to exposure to wind or sun

Warnings

For external use only

- Do not use this productif solution changes color or becomes cloudy

When using this product

- remove contact lens before using
- to avoid contamination, do not touch tip of container to any surface
- replace cap after using. Keep container tightly closed

Stop use and ask a doctor if you experience

- eye pain
- changes in vision
- continued redness or irritation of the eye or if the condition worsens or persists for more than 72 hours

KEEP OUT OF REACH OF CHILDREN

Keep out of the reach of children. If accidentally swallowed, get medical help or contact a Poison Control Center (1-800-222-1222) immediately.

Directions

Instill 1 or 2 drops in the affected eye(s) as needed.

Other information

- Store at 59°-86°F (15°-30°C)

Inactive ingredients

benzalkonium chloride, dextrose, edetate disodium, potassium chloride, purified water, sodium bicarbonate, sodium chloride, sodium citrate, sodium phosphate dibasic, and sodium phosphate monobasic